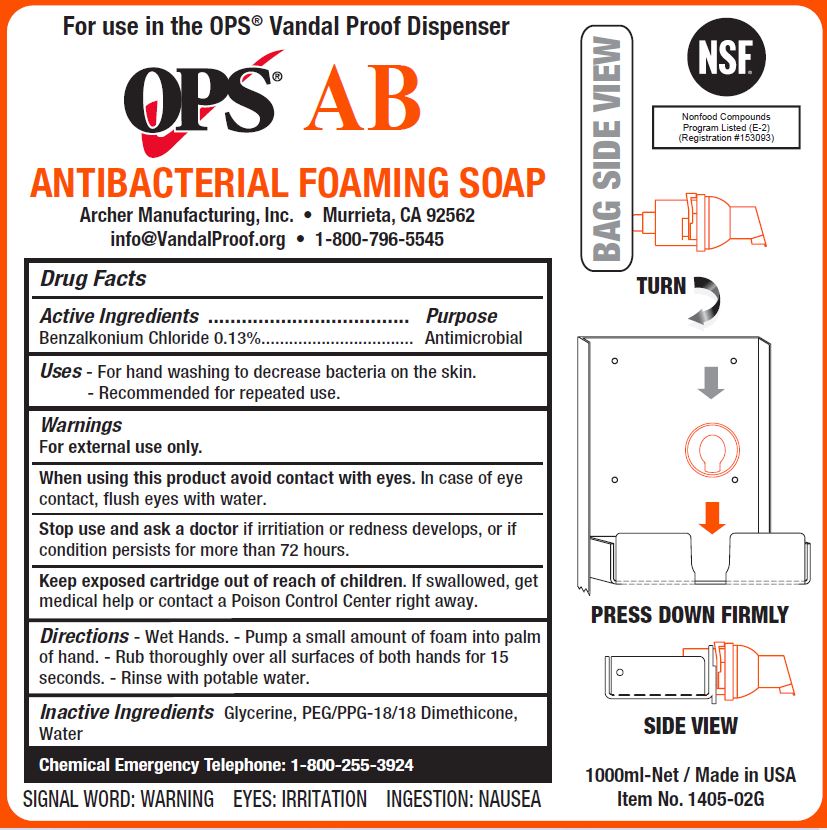 DRUG LABEL: OPS AB ANTIBACTERIAL FOAMING
NDC: 79016-140 | Form: SOAP
Manufacturer: Archer Manufacturing, Inc.
Category: otc | Type: HUMAN OTC DRUG LABEL
Date: 20241205

ACTIVE INGREDIENTS: BENZALKONIUM CHLORIDE 0.0013 mg/1 mL
INACTIVE INGREDIENTS: WATER; GLYCERIN; PEG/PPG-18/18 DIMETHICONE

ARCHER - OPS AB ANTIBACTERIAL FOAMING SOAP (79016-140)

Active Ingredient

Benzalkonium Chloride 0.13%

Purpose

Antimicrobial

INDICATIONS AND USAGE

Uses• For hand washing to decrease bacteria on skin. • Recommended for repeated use.

Warnings

For external use only.

When using this product avoid contact with eyes. In case of eye contact, flush eyes with water.

Stop use and ask a doctor if irritation or redness develops, or if condition persists for more than 72 hours.

Keep out of reach of children.If swallowed, get medical help or contact a Poison Control Center right away.

DOSAGE AND ADMINISTRATION

Directions• Place a small amount of soap onto palm of wet hand or hands. • Rub hands together for 20 seconds. • Rinse with potable water.

Inactive Ingredients

Water, coco-glucoside, laurtrimonium chloride, cocamidopropylamine oxide, citric acid.

Manufactured for ARCHER Manufacturing, Inc.

Murrieta, CA 92562 • info@VandalProof.org • 1-800-796-5545

For hand washing to decrease bacteria on skin.

Made in USA